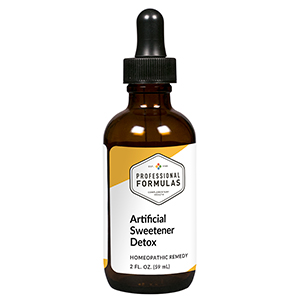 DRUG LABEL: Artificial Sweetener Detox
NDC: 63083-6034 | Form: LIQUID
Manufacturer: Professional Complementary Health Formulas
Category: homeopathic | Type: HUMAN OTC DRUG LABEL
Date: 20190815

ACTIVE INGREDIENTS: ASPARTAME 6 [hp_X]/59 mL; SACCHARIN 6 [hp_X]/59 mL; SUCRALOSE 6 [hp_X]/59 mL; SODIUM CYCLAMATE 30 [hp_X]/59 mL
INACTIVE INGREDIENTS: ALCOHOL; WATER

X34

ACTIVE INGREDIENTS

Aspartame 6X, 12X, 30X, 60X, 100X
Saccharin 6X, 12X, 30X, 60X, 100X
Sucralose 6X, 12X, 30X, 60X, 100X
Sodium cyclamate 30X, 60X, 100X

QUESTIONS

Professional Formulas

PO Box 2034 Lake Oswego, OR 97035

INDICATIONS

For the temporary relief of occasional headache, bloating, nausea or vomiting, diarrhea, difficulty breathing, cough, runny nose, skin irritation, itchy eyes, or irritability due to sensitivity to or exposure to artificial sweeteners.*

PURPOSE

*Claims based on traditional homeopathic practice, not accepted medical evidence. Not FDA evaluated.

WARNINGS

Consult a doctor if condition worsens or symptoms persist. Keep out of the reach of children. In case of overdose, get medical help or contact a poison control center right away. If pregnant or breastfeeding, ask a healthcare professional before use.

Keep out of the reach of children.

PREGNANCY OR BREAST FEEDING

If pregnant or breastfeeding, ask a healthcare professional before use.

DIRECTIONS

Place drops under tongue 30 minutes before/after meals. Adults and children 12 years and over: Take 10 drops up to 3 times per day. Consult a physician for use in children under 12 years of age.

OTHER INFORMATION

Tamper resistant. If seal is broken, do not use. After opening, close container tightly and store at room temperature away from heat.

INACTIVE INGREDIENTS

20% ethanol, purified water.

LABEL

Est 1985

Professional Formulas

Complementary Health

Artificial Sweetener Detox

Homeopathic Remedy

2 FL. OZ. (59 mL)